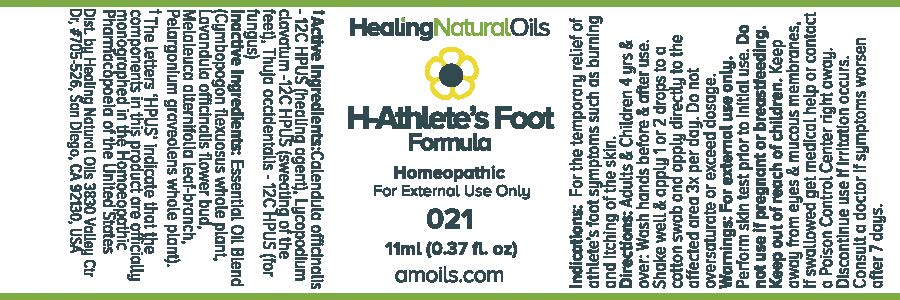 DRUG LABEL: H-Athletes Foot Formula
NDC: 61077-021 | Form: OIL
Manufacturer: Healing Natural Oils LLC
Category: homeopathic | Type: HUMAN OTC DRUG LABEL
Date: 20171227

ACTIVE INGREDIENTS: CALENDULA OFFICINALIS FLOWERING TOP 12 [hp_C]/11 mL; LYCOPODIUM CLAVATUM SPORE 12 [hp_C]/11 mL; THUJA OCCIDENTALIS LEAFY TWIG 12 [hp_C]/11 mL
INACTIVE INGREDIENTS: CYMBOPOGON FLEXUOSUS WHOLE; LAVANDULA ANGUSTIFOLIA FLOWER; MELALEUCA ALTERNIFOLIA LEAF; PELARGONIUM GRAVEOLENS WHOLE; ALCOHOL

Active Ingredients:

Calendula officinalis-12C HPUS,
Lycopodium clavatum -12C HPUS,
Thuja occidentalis 12C HPUS

Purpose

Calendula officinalis -12C HPUS (healing agent),
Lycopodium clavatum -12C HPUS (sweating of the feet),
Thuja occidentalis 12C HPUS (for fungus)
The letters ‘HPUS’ indicate that the components in this product are officially
monographed in the Homoeopathic Pharmacopoeia of the United States

Inactive Ingredients:

Essential Oil Blend (Cymbopogon flexuosus whole plant
Lavandula officinalis flower bud, Melaleuca
alternifolia leaf-branch, Pelargonium
graveolens whole plant), Ethanol

Indications:

For the temporary relief of athlete's foot symptoms such as burning and itching of the skin.

Directions:

Adults and Children 4 yrs and over: Wash hands before and after use.
Shake well and apply 1 or 2 drops to a cotton swab and apply directly to the affected area 3x per day.
Do not oversaturate or exceed dosage.

Warnings:

For external use only.

Perform skin test prior to initial use.

Do not use if pregnant or breastfeeding.

Keep out of reach of children.

OTHER SAFETY INFORMATION

Keep away from eyes and mucous membranes. If swallowed get medical help
or contact a Poison Control Center right away.

Discontinue use if irritation occurs.

ASK DOCTOR

Consult a doctor if symptoms worsen after 7 days.

DESCRIPTION

Dist. by Healing Natural Oils 3830 Valley Ctr Dr, #705-526, San Diego, CA 92130, USA

PACKAGE LABEL

Healing Natural Oils

H-Athlete's Foot
Formula

Homeopathic

For External Use Only

021

11ml (0.37 fl. oz)
amoils.com